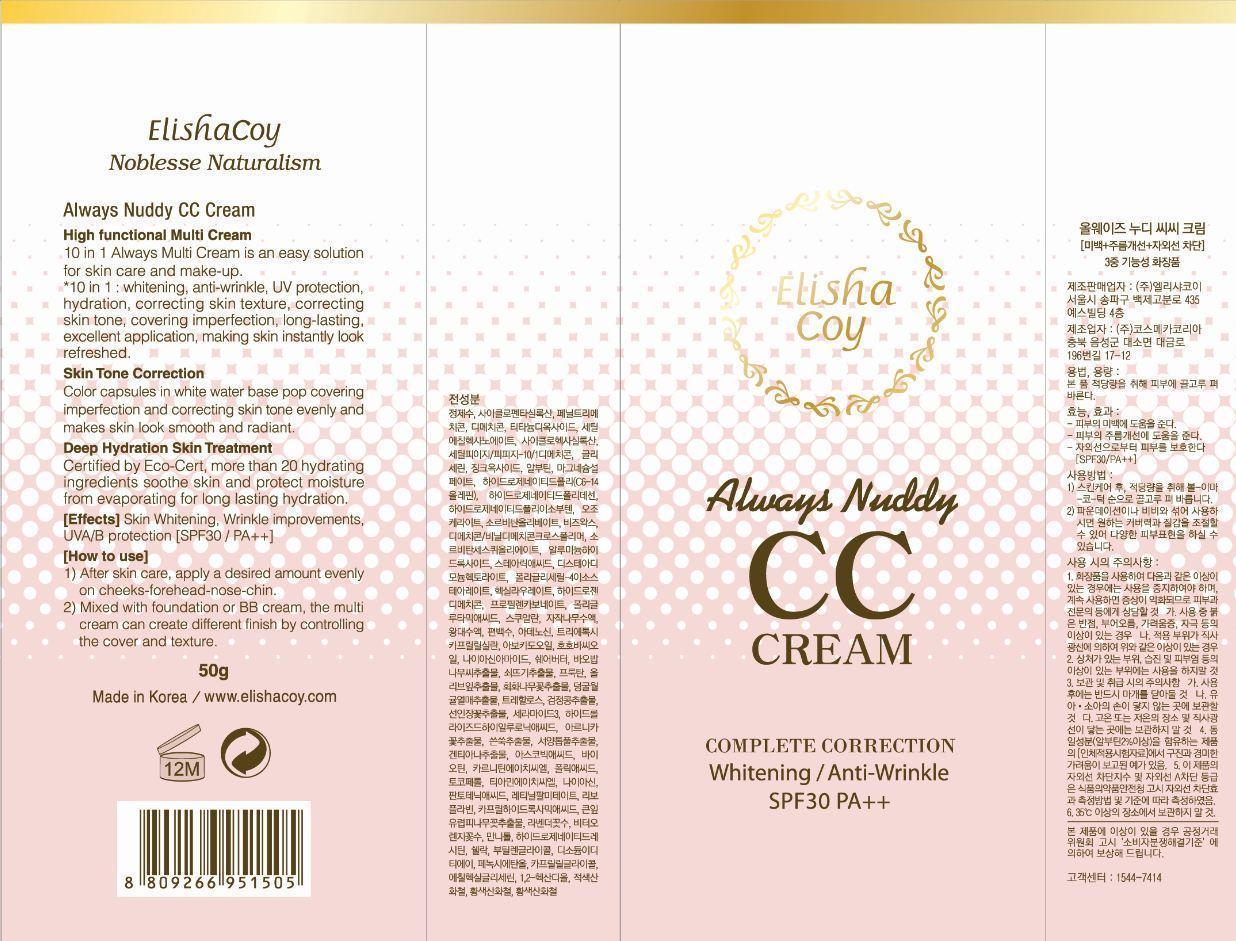 DRUG LABEL: Always Nuddy CC
NDC: 53727-104 | Form: CREAM
Manufacturer: Cosmecca Korea Co., Ltd.
Category: otc | Type: HUMAN OTC DRUG LABEL
Date: 20140815

ACTIVE INGREDIENTS: TITANIUM DIOXIDE 4 g/50 g; ZINC OXIDE 1 g/50 g
INACTIVE INGREDIENTS: WATER; CYCLOMETHICONE 5; DIMETHICONE; BUTYLENE GLYCOL DICAPRYLATE/DICAPRATE; PHENYL TRIMETHICONE; CETYL PEG/PPG-10/1 DIMETHICONE (HLB 2); GLYCERIN; METHYL HYDROGENATED ROSINATE; CYCLOMETHICONE 6; CETYL ETHYLHEXANOATE; ARBUTIN; MAGNESIUM SULFATE; MICA; CERESIN; POLYGLYCERYL-4 ISOSTEARATE; DIMETHICONE/VINYL DIMETHICONE CROSSPOLYMER (HARD PARTICLE); HEXYL LAURATE; DISTEARDIMONIUM HECTORITE; ALUMINUM HYDROXIDE; STEARIC ACID; CAPRYLYL GLYCOL; HYDROGENATED POLYDECENE (550 MW); HYDROGENATED POLYBUTENE (370 MW); MANNITOL; YELLOW WAX; PHENOXYETHANOL; ETHYLHEXYLGLYCERIN; PROPYLENE CARBONATE; HYDROGEN; SQUALANE; SORBITAN SESQUIOLEATE; SORBITAN OLIVATE; 1,2-HEXANEDIOL; ADENOSINE; SHELLAC; HYDROGENATED SOYBEAN LECITHIN; BUTYLENE GLYCOL; PHYLLOSTACHYS RETICULATA RESIN; CHAMAECYPARIS OBTUSA WHOLE; BETULA PLATYPHYLLA VAR. JAPONICA RESIN; METHICONE (20 CST); EDETATE DISODIUM; TRIETHOXYCAPRYLYLSILANE; TREHALOSE; JOJOBA OIL; AVOCADO OIL; NIACINAMIDE; HYALURONIC ACID; CERAMIDE 3; SHEA BUTTER; TILIA PLATYPHYLLOS FLOWER; LAVANDULA ANGUSTIFOLIA FLOWER; CITRUS AURANTIUM FLOWER; ALCOHOL; SOYBEAN SEED OIL; OPUNTIA FICUS-INDICA; CRANBERRY; OLEA EUROPAEA LEAF; EQUISETUM ARVENSE WHOLE; ADANSONIA DIGITATA SEED OIL; POLYGLYCOLIC ACID; GENTIANA LUTEA ROOT; ARTEMISIA ABSINTHIUM WHOLE; ARNICA MONTANA FLOWER; ACHILLEA MILLEFOLIUM; STYPHNOLOBIUM JAPONICUM FLOWER; FRUCTOSE; CITRIC ACID MONOHYDRATE; POTASSIUM SORBATE; SODIUM BENZOATE; CAPRYLHYDROXAMIC ACID; TOCOPHEROL; THIAMINE HYDROCHLORIDE; RIBOFLAVIN; VITAMIN A PALMITATE; PANTOTHENIC ACID; NIACIN; FOLIC ACID; CARNITINE HYDROCHLORIDE, (+)-; BIOTIN; ASCORBIC ACID; FERRIC OXIDE RED

ACTIVE INGREDIENT

Titanium Dioxide (7%), Zinc Oxide (2.88%)

PURPOSE

Always Nuddy CC Cream

Complete Correction

Whitening/Anti-Wrinkle

SPF30 PA++

Keep out of reach of children

INDICATIONS AND USAGE

ElishaCoy

Noblesse Naturalism

Always Nuddy CC Cream

High functional Multi Cream

10 in 1 Always Multi Cream is an easy solution for skin care and make-up.

*10 in 1 : whitening, anti-wrinkle, UV protection, hydration, correcting skin texture, correcting skin tone, covering imperfection, long-lasting, excellent application, making skin instantly look refreshed.

Skin Tone Correction

Color Capsules in white water base pop covering imperfection and correcting skin tone evenly and makes skin look smooth and radiant.

Deep Hydration Skin Treatment

Certified by Eco-Cert, more than 20 hydrating ingredients soothe skin and protect moisture from evaporating for long lasting hydration.

[Effects] Skin Whitening, Wrinkle improvements, UVA/B Protection [SPF10 / PA++]

Warnings

DOSAGE AND ADMINISTRATION

[How to Use]

1) After skin care, apply a desired amount evenly on cheeks-forehead-nose-chin.

2) Mixed with foundation or BB cream, the multi cream can create different finish by controlling the cover and texture.

INACTIVE INGREDIENT

Water, Cyclopentasiloxane, Dimethicone, Butylene Glycol Dicaprylate/Dicaprate, Phenyl Trimethicone, Cetyl PEG/PPG-10/1 Dimethicone, Glycerin, Methyl Hydrogenated Rosinate, Cyclohexasiloxane, Cetyl Ethylhexanoate, Arbutin, Magnesium Sulfate, Mica, Ozokerite, Polyglyceryl-4 Isostearate, Dimethicone/Vinyl Dimethicone Crosspolymer, Hexyl Laurate, Disteardimonium Hectorite, Aluminum Hydroxide, Stearic Acid, Caprylyl Glycol, Hydrogenated Poly(C6-14 Olefin), Hydrogenated Polyisobutene, Hydrogenated Polydecene, Mannitol, Beeswax, Phenoxyethanol, Ethylhexylglycerin, Propylene Carbonate, Hydrogen Dimethicone, Squalane, Sorbitan Sesquioleate, Sorbitan Olivate, 1,2-Hexanediol, Adenosine, Shellac, Hydrogenated Lecithin, Butylene Glycol, Phyllostachis Bambusoides Juice, Chamaecyparis Obtusa Water, Betula Platyphylla Japonica Juice, Methicone, Disodium EDTA, Triethoxycaprylylsilane, Trehalose, Jojoba Seed Oil, Avocado Oil, Niacinamide, Hydrolyzed Hyaluronic Acid, Ceramide 3, Shea Butter, Tilia Platyphyllos Flower Extract, Lavender Flower Water, Citrus Bitter Orange (Aurantium amara) Flower Water, Alcohol, Soybean (Glycine Soja) Seed Extract, Opuntia Ficus-Indica Extract, Cranberry Fruit Extract, Olive Leaf Extract, Equisetum Arvense Extract, Baobab Tree (Adansonia Digitata) Seed Extract, Polyglutamic Acid, Gentiana Lutea Root Extract, Artemisia Absinthium Extract, Arnica Montana Flower Extract, Yarrow (Achillea Millefolium) Extract, Sophora Japonica Flower Extract, Fructan, Citric Acid, Potassium sorbate, Sodium Benzoate, Caprylhydroxamic Acid, Tocopherol, Thiamine HCl, Riboflavin, Retinyl Palmitate, Pantothenic Acid, Niacin, Folic Acid, Carnitine HCl, Biotin, Ascorbic Acid, Iron Oxides (CI 77492, CI 77491)